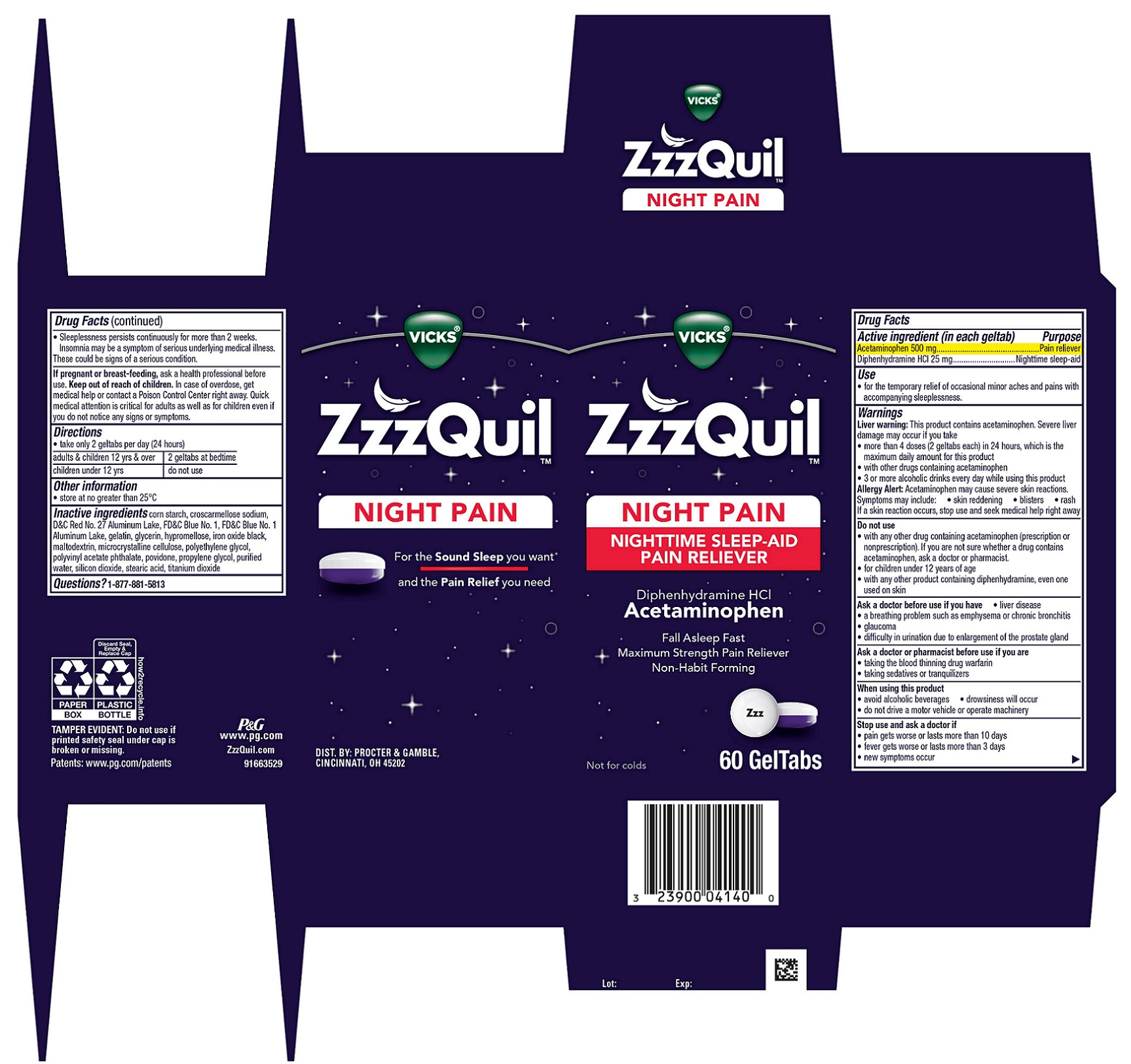 DRUG LABEL: Vicks ZzzQuil
NDC: 37000-974 | Form: TABLET, COATED
Manufacturer: The Procter & Gamble Manufacturing Company
Category: otc | Type: HUMAN OTC DRUG LABEL
Date: 20251120

ACTIVE INGREDIENTS: DIPHENHYDRAMINE HYDROCHLORIDE 25 mg/1 1; ACETAMINOPHEN 500 mg/1 1
INACTIVE INGREDIENTS: POLYVINYL ACETATE PHTHALATE; FD&C BLUE NO. 1 ALUMINUM LAKE; PROPYLENE GLYCOL; STEARIC ACID; FERROSOFERRIC OXIDE; FD&C BLUE NO. 1; GELATIN; GLYCERIN; POLYETHYLENE GLYCOL, UNSPECIFIED; WATER; D&C RED NO. 27 ALUMINUM LAKE; STARCH, CORN; TITANIUM DIOXIDE; HYPROMELLOSE, UNSPECIFIED; MALTODEXTRIN; CROSCARMELLOSE SODIUM; MICROCRYSTALLINE CELLULOSE; POVIDONE; SILICON DIOXIDE

Vicks ZzzQuil Night Pain GelTabs

Drug Facts

Active ingredients (in each geltab)

Acetaminophen 500 mg

Diphenhydramine HCl 25 mg

Purpose

Pain reliever

Nighttime sleep-aid

Uses

- for the temporary relief of occasional minor aches and pains with accompanying sleeplessness.

Warnings

Liver warning:

This product contains acetaminophen. Severe liver damage may occur if

• adult takes more than 4 doses (2 geltabs each) in 24 hrs, which is the maximum daily amount for this product

• taken with other drugs containing acetaminophen

• 3 or more alcoholic drinks every day while using this product

Allergy Alert:

Acetaminophen may cause severe skin reactions.

Symptoms may include:

- skin reddening
- blisters
- rash

If a skin reaction occurs, stop use and seek medical help right away

Do not use

- with any other drug containing acetaminophen (prescription or nonprescription). If you are not sure whether a drug contains acetaminophen, ask a doctor or pharmacist.
- for children under 12 years of age
- with any other product containing diphenhydramine, even one used on skin.

Ask a doctor before use if you have

- liver disease
- a breathing problem such as emphysema or chronic bronchitis
- glaucoma
- difficulty in urination due to enlargement of the prostate gland

Ask a doctor or pharmacist before use if you are

- taking the blood thinning drug warfarin
- taking sedatives or tranquilizers

When using this product

- avoid alcoholic beverages
- drowsiness will occur
- do not drive a motor vehicle or operate machinery

Stop use and ask a doctor if

- pain gets worse or lasts more than 10 days
- fever gets worse or lasts more than 3 days
- new symptoms occur
- sleeplessness persists continuously for more than 2 weeks. Insomnia may be a symptom of serious underlying medical illness.

These could be signs of a serious condition.

PREGNANCY OR BREAST FEEDING

If pregnant or breast-feeding, ask a health professional before use.

Keep out of reach of children.

OVERDOSAGE

In case of overdose, get medical help or contact a Poison Control Center right away. Quick medical attention is critical for adults as well as for children even if you do not notice any signs or symptoms.

Directions

- take only 2 geltabs per day (24 hours)

adults & children 12 yrs & over | 2 geltabs at bedtime
children under 12 yrs | do not use

Other information

- store at no greater than 25° C

Inactive ingredients

corn starch, croscarmellose sodium, D&C Red No. 27 Aluminum Lake, FD&C Blue No. 1, FD&C Blue No. 1 Aluminum Lake, gelatin, glycerin, hypromellose, iron oxide black, maltodextrin, microcrystalline cellulose, polyethylene glycol, polyvinyl acetate phthalate, povidone, propylene glycol, purified water, silicon dioxide, stearic acid, titanium dioxide

Questions?

1-877-881-5813

TAMPER EVIDENT: Do not use if printed safety seal under cap is broken or missing.

DIST. BY PROCTER & GAMBLE,

CINCINNATI, OH 45202

PRINCIPAL DISPLAY PANEL - 60 GelTab Carton

VICKS®

ZzzQuil™
NIGHT PAIN
NIGHTTIME SLEEP-AID

PAIN RELIEVER
Diphenhydramine HCl

Acetaminophen

- Fall Asleep Fast
- Max Strength Pain Reliever
- Non-Habit Forming

Not for colds.

60 GelTabs